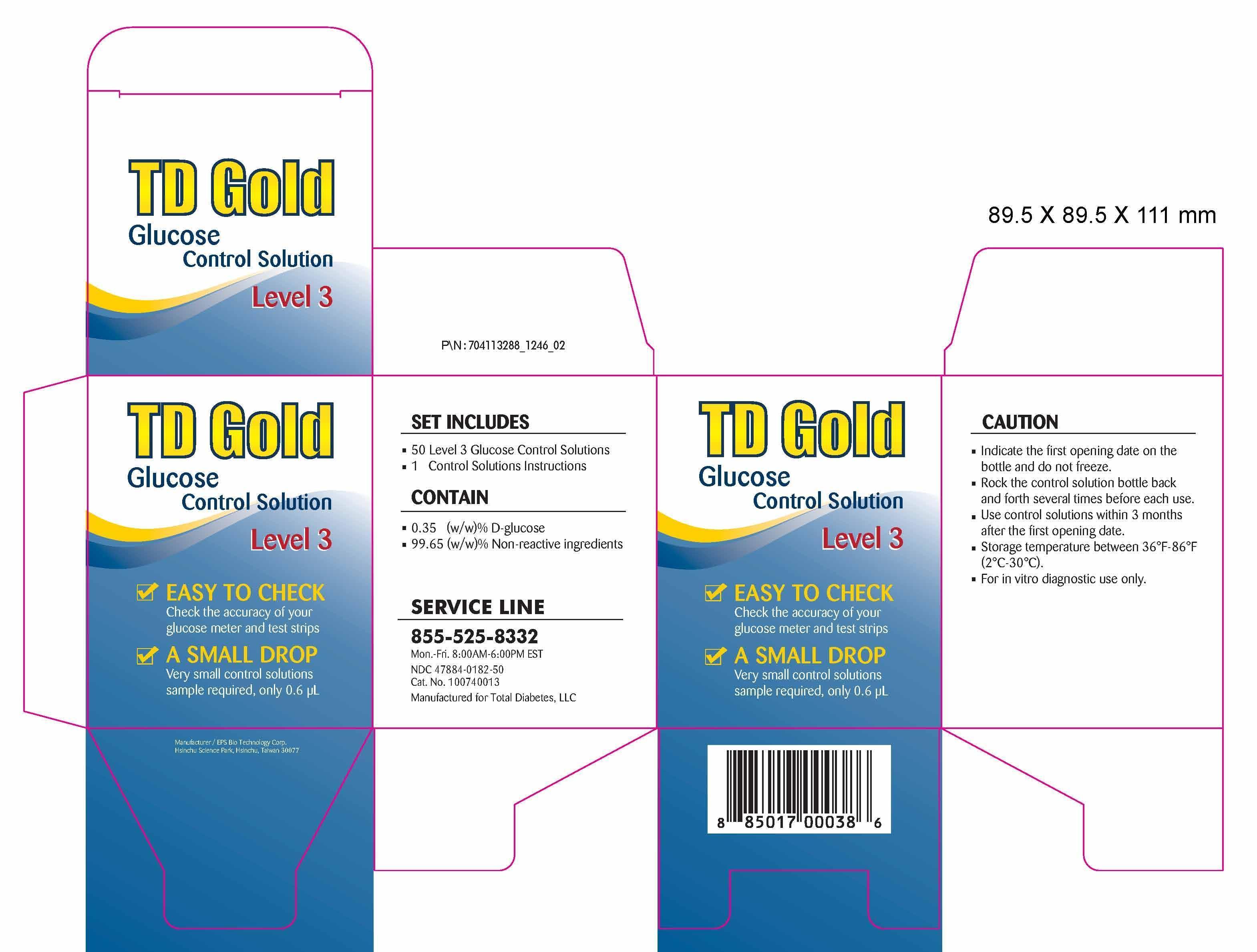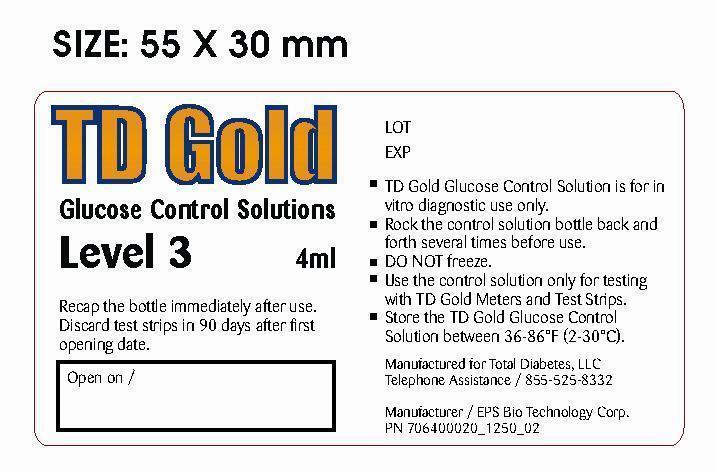 DRUG LABEL: 50 TD Gold Glucose Control Solution Level 3 Set
NDC: 47884-182
Manufacturer: EPS Bio Technology Corp.
Category: other | Type: MEDICAL DEVICE
Date: 20131023

Home Use Medical Device- 50 TD Gold Glucose Control Solution Level 3